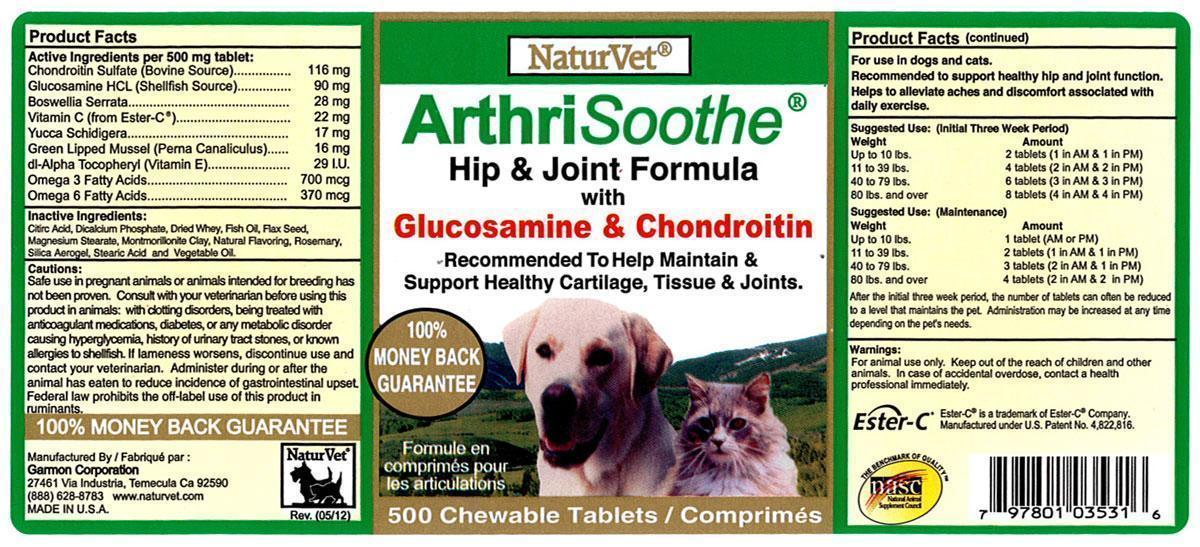 DRUG LABEL: NaturVet ArthriSoothe
NDC: 27135-0353 | Form: TABLET, CHEWABLE
Manufacturer: The Garmon Corporation
Category: animal | Type: OTC ANIMAL DRUG LABEL
Date: 20140328

ACTIVE INGREDIENTS: CHONDROITIN SULFATE (BOVINE) 116 mg/1 1; GLUCOSAMINE HYDROCHLORIDE 90 mg/1 1; INDIAN FRANKINCENSE 28 mg/1 1; CALCIUM ASCORBATE 22 mg/1 1; YUCCA SCHIDIGERA 17 mg/1 1; NEW ZEALAND GREEN MUSSEL 16 mg/1 1; .ALPHA.-TOCOPHEROL ACETATE 29 [iU]/1 1; OMEGA-3 FATTY ACIDS 0.700 mg/1 1; OMEGA-6 FATTY ACIDS 0.370 mg/1 1
INACTIVE INGREDIENTS: CITRIC ACID MONOHYDRATE; CALCIUM PHOSPHATE, DIBASIC, ANHYDROUS; WHEY; FISH OIL; FLAX SEED; MAGNESIUM STEARATE; MONTMORILLONITE; ROSEMARY; SILICON DIOXIDE; STEARIC ACID; CORN OIL

NaturVet ArthriSoothe Tablets

Product Facts

Active Ingredients per 500 mg tablet:

Chondroitin Sulfate (Bovine Source)........................................... 116 mg

Glucosamine HCl (Shellfish Source)............................................ 90 mg

Boswellia Serrata........................................................................ 28 mg

Calcium Ascorbate (from Ester C*)............................................... 22 mg

Yucca Schidigera........................................................................ 17 mg

Green Lipped Mussel (Perna Canaliculus)..................................... 16 mg

dl-Alpha Tocopheryl (Vitamin E)................................................... 29 I.U.

Omega 3 Fatty Acids............................................................... 370 mcg

Omega 6 Fatty Acids............................................................... 700 mcg

Inactive Ingredients:

Citric Acid, Dicalcium Phosphate, Dried Whey, Fish Oil, Flax Seed,

Magnesium Stearate, Montmorillonite Clay, Natural Flavoring, Rosemary

Silical Aerogel, Stearic Acid and Vegetable Oil.

PRECAUTIONS

Cautions:

Safe use in pregnant animals or animals intended for breeding has

Not been proven. Consult with your veterinarian before using this

product in animals: with clotting disorders, being treated with

anticoagulant medications, diabetes, or any metabolic disorder

causing hypoglycemia, history of urinary tract stones, or known

allergies to shellfish. If lameness worsens, discontinue use and

contact your veterinarian. Administer during or after the

animal has eaten to reduce incidence of gastrointestinal upset.

Federal law prohibits the off-label use of this product in ruminants.

DESCRIPTION

For use in dogs and cats.

Recommended to support healthy hip and joint function.

Helps to alleviate aches and discomfort associated with

daily exercise.

DOSAGE AND ADMINISTRATION

Suggested Use: (Initial Three Week Period)

Weight Amount

Up to 10 lbs. 2 tablets (1 in AM & 1 in PM)

11 to 39 lbs. 4 tablets (2 in AM & 2 in PM)

40 to 79 lbs. 6 tablets (3 in AM & 3 in PM)

80 lbs. and over 9 tablets (4 in AM & 4 in PM)

Suggested Use: (Maintenance)

Weight Amount

Up to 10 lbs. 1 tablet (AM or PM)

11 to 39 lbs. 2 tablets (1 in AM & 1 in PM)

40 to 79 lbs. 3 tablets (2 in AM & 1 in PM)

80 lbs. and over 4 tablets (2 in AM & 2 in PM)

After the initial three week period, the number of tablets can be reduced

to a level that maintains the pet. Administration may be increased at any time

depending on the pet's needs.

Warnings:

For animal use only. Kept out of the reach of children and other

Animals. In case of accidental overdose, contact a health

professional immediately.